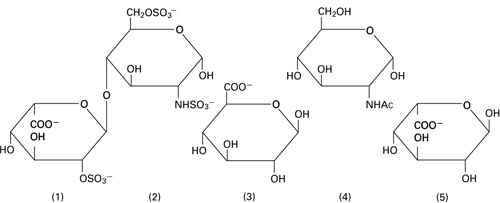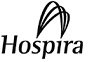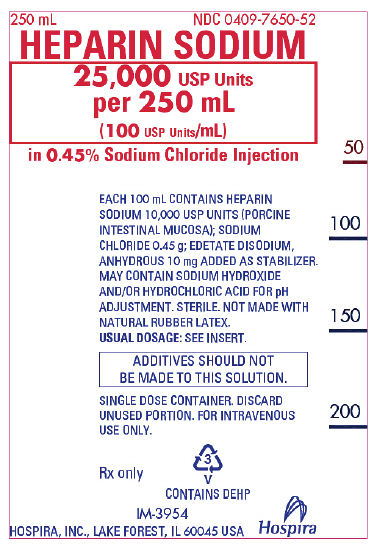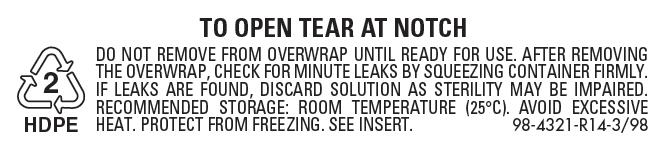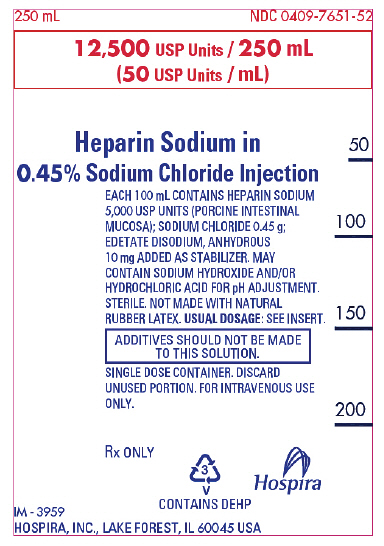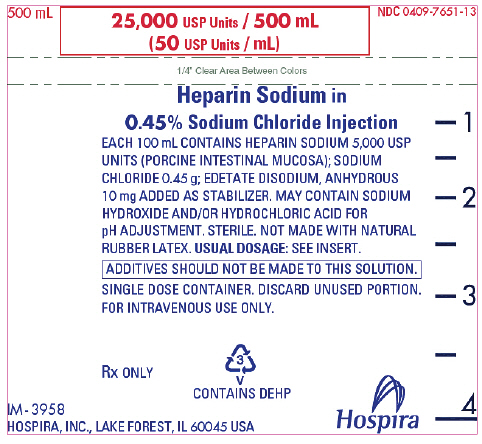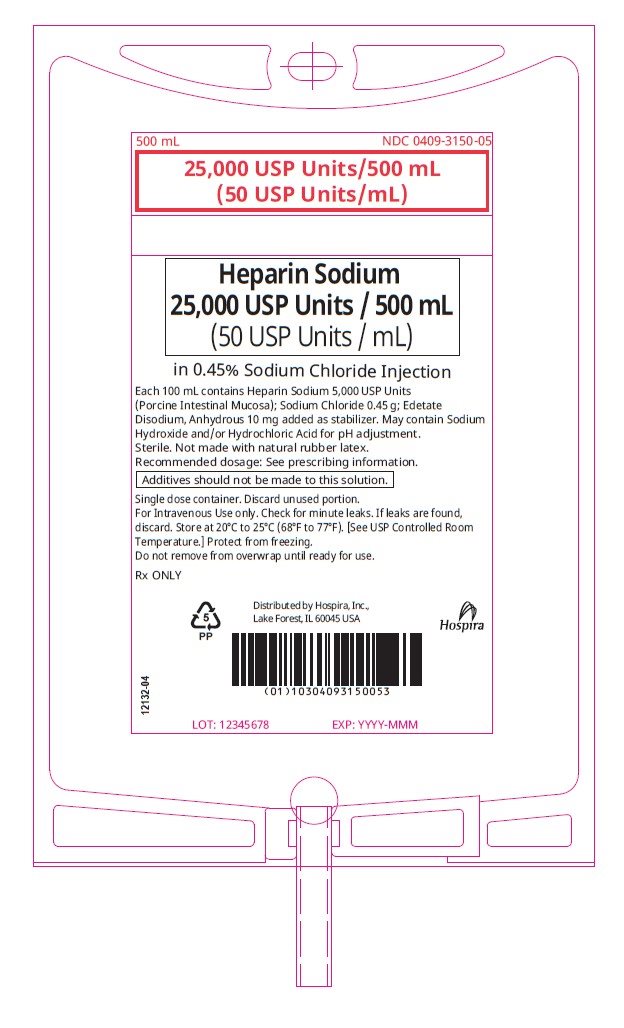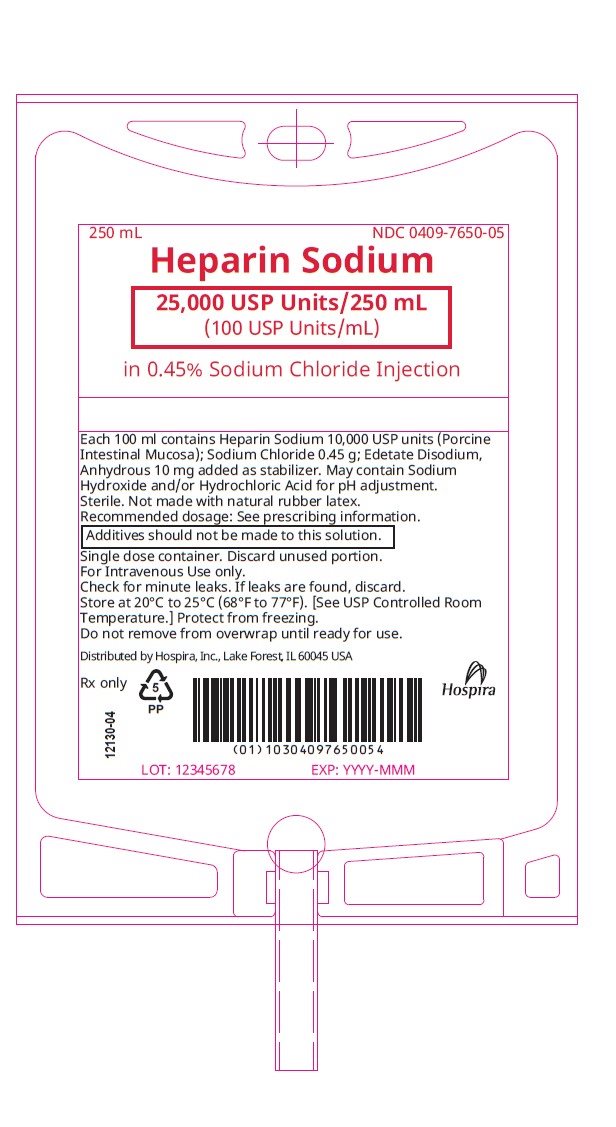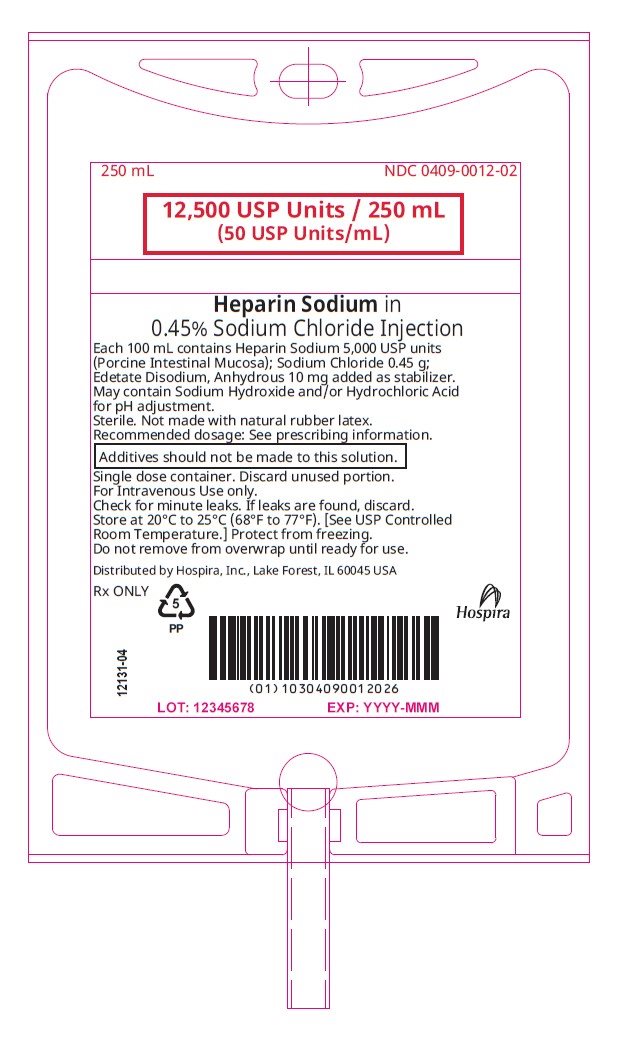 DRUG LABEL: Heparin Sodium
NDC: 0409-7650 | Form: INJECTION, SOLUTION
Manufacturer: Hospira, Inc.
Category: prescription | Type: HUMAN PRESCRIPTION DRUG LABEL
Date: 20251202

ACTIVE INGREDIENTS: HEPARIN SODIUM 10000 [USP'U]/100 mL
INACTIVE INGREDIENTS: SODIUM CHLORIDE 0.45 g/100 mL; EDETATE DISODIUM ANHYDROUS 10 mg/100 mL; SODIUM HYDROXIDE; HYDROCHLORIC ACID; WATER

HIGHLIGHTS OF PRESCRIBING INFORMATION

These highlights do not include all the information needed to use HEPARIN SODIUM IN SODIUM CHLORIDE INJECTION safely and effectively. See full prescribing information for HEPARIN SODIUM IN SODIUM CHLORIDE INJECTION.
HEPARIN SODIUM IN SODIUM CHLORIDE INJECTION, for intravenous use
Initial U.S. Approval: 1939

RECENT MAJOR CHANGES

Warnings and Precautions, Unresponsiveness to Heparin with; Concomitant Use with Andexanet Alfa (5.4) | 11/2025

1 INDICATIONS AND USAGE

HEPARIN SODIUM IN SODIUM CHLORIDE INJECTION is indicated for: (1)

- Prophylaxis and treatment of venous thrombosis and pulmonary embolism
- Prophylaxis and treatment of thromboembolic complications associated with atrial fibrillation
- Treatment of acute and chronic consumption coagulopathies (disseminated intravascular coagulation)
- Prevention of clotting in arterial and cardiac surgery
- Prophylaxis and treatment of peripheral arterial embolism
- Anticoagulant use in blood transfusions, extracorporeal circulation and dialysis procedures

2 DOSAGE AND ADMINISTRATION

Recommended Adult Dosages:

- Therapeutic Anticoagulant Effect with Full-Dose Heparin* (2.3)

Intermittent Intravenous Injection | Initial Dose | 10,000 Units
Intermittent Intravenous Injection | Every 4 to 6 hours | 5,000 Units to 10,000 Units
Continuous Intravenous Infusion | Initial Dose | 5,000 Units
Continuous Intravenous Infusion | Continuous | 20,000 Units to 40,000 Units/24 hours
*Based on 150 lb (68 kg) patient.

- Cardiovascular Surgery (2.5)

Intravascular via Total Body Perfusion | Initial Dose | Not less than 150 units/kg; adjust for longer procedures

- Extracorporeal Dialysis (2.8)

Intravascular via Extracorporeal Dialysis | Follow equipment manufacturer's operating directions carefully.
For pediatric dosing see section 2.4 of full prescribing information.

3 DOSAGE FORMS AND STRENGTHS

HEPARIN SODIUM in 0.45% Sodium Chloride Injection is available as: (3)

- Injection: 25,000 USP Units/250 mL (100 USP Units/mL) in clear solution in single-dose flexible plastic container
- Injection: 12,500 USP Units/250 mL (50 USP Units/mL) in clear solution in single-dose flexible plastic container
- Injection: 25,000 USP Units/500 mL (50 USP Units/mL) in clear solution in single-dose flexible plastic container

4 CONTRAINDICATIONS

- History of Heparin-induced Thrombocytopenia (HIT) (With or Without Thrombosis) (4)
- Known hypersensitivity to heparin or pork products (4)
- In whom suitable blood coagulation tests cannot be performed at appropriate intervals (4)
- With an uncontrollable active bleeding state, except when treating disseminated intravascular coagulation (4)

5 WARNINGS AND PRECAUTIONS

- Fatal Medication Errors: Confirm choice of correct strength prior to administration (5.1)
- Hemorrhage: Fatal cases have occurred. Use caution in conditions with increased risk of hemorrhage (5.2)
- HIT (With or Without Thrombosis): Monitor for signs and symptoms and discontinue if indicative of HIT (With or Without Thrombosis) (5.3)
- Monitoring: Blood coagulation tests guide therapy for full-dose heparin.
  Monitor platelet count and hematocrit in all patients receiving heparin (5.6)
- Hyperkalemia: Measure blood potassium in patients at risk of hyperkalemia before starting heparin therapy and periodically in all patients (5.9)

6 ADVERSE REACTIONS

Most common adverse reactions are hemorrhage, thrombocytopenia, HIT (With or Without Thrombosis), local irritation, hypersensitivity reactions, and elevations of aminotransferase levels. (6.1)

To report SUSPECTED ADVERSE REACTIONS, contact Pfizer Inc. at 1-800-438-1985 or FDA at 1-800-FDA-1088 or www.fda.gov/medwatch.

7 DRUG INTERACTIONS

- Drugs that interfere with coagulation, platelet aggregation or drugs that counteract coagulation may induce bleeding (7)
- Andexanet alfa may reduce the efficacy of heparin when used concomitantly (7.3)

FULL PRESCRIBING INFORMATION

1 INDICATIONS AND USAGE

HEPARIN SODIUM IN SODIUM CHLORIDE INJECTION is indicated for:

- Prophylaxis and treatment of venous thrombosis and pulmonary embolism;
- Prophylaxis and treatment of thromboembolic complications associated with atrial fibrillation;
- Treatment of acute and chronic consumption coagulopathies (disseminated intravascular coagulation);
- Prevention of clotting in arterial and cardiac surgery;
- Prophylaxis and treatment of peripheral arterial embolism;
- Anticoagulant use in blood transfusions, extracorporeal circulation, and dialysis procedures.

2 DOSAGE AND ADMINISTRATION

2.1 Preparation for Administration

Confirm the selection of the correct formulation and strength prior to administration of the drug.

Do not use HEPARIN SODIUM IN SODIUM CHLORIDE INJECTION as a "catheter lock flush" product.

Administer this product by intravenous infusion.

Do not admix with other drugs.

This product should not be infused under pressure.

Parenteral drug products should be inspected visually for particulate matter and discoloration prior to administration, whenever solution and container permit.

Do not administer unless the solution is clear and container is undamaged.

Discard unused portion.

To Open

Tear outer wrap and remove solution container. For PVC bags, some opacity of the plastic due to moisture absorption during the sterilization process may be observed. This is normal and does not affect the solution quality or safety. The opacity will diminish gradually.

(Use aseptic technique)

1. Close flow control clamp of administration set.
2. Remove cover from outlet port at bottom of container.
3. Insert piercing pin of administration set into port with a twisting motion until the set is firmly seated.
  NOTE: See full directions on administration set carton.
4. Suspend container from hanger.
5. Squeeze and release drip chamber to establish proper fluid level in chamber.
6. Open flow control clamp and clear air from set. Close clamp.
7. Attach set to venipuncture device. If device is not indwelling, prime and make venipuncture.
8. Regulate rate of administration with flow control clamp.

Warning: Do not use flexible container in series connections.

2.2 Laboratory Monitoring for Efficacy and Safety

The dosage of heparin sodium should be adjusted according to the patient's coagulation test results. When heparin is given by continuous intravenous infusion, the coagulation time should be determined approximately every 4 hours in the early stages of treatment. When the drug is administered intermittently by intravenous injection, coagulation tests should be performed before each injection during the early stages of treatment and at appropriate intervals thereafter. Dosage is considered adequate when the activated partial thromboplastin time (APTT) is 1.5 to 2 times normal or when the whole blood clotting time is elevated approximately 2.5 to 3 times the control value.

Periodic platelet counts, hematocrits, and tests for occult blood in stool are recommended during the entire course of heparin therapy.

2.3 Therapeutic Anticoagulant Effect With Full-Dose Heparin

The dosing recommendations in Table 1 are based on clinical experience. Although dosage must be adjusted for the individual patient according to the results of suitable laboratory tests, the following dosage schedules may be used as guidelines:

Table 1: Recommended Adult Full-Dose Heparin Regimens for Therapeutic Anticoagulant Effect
Method of Administration | Frequency | Recommended Dose [Based on 150 lb. (68 kg) patient.]
Intermittent Intravenous Injection | Initial Dose | 10,000 Units
Intermittent Intravenous Injection | Every 4 to 6 hours | 5,000 Units to 10,000 Units
Continuous Intravenous Infusion | Initial Dose | 5,000 Units by intravenous injection
Continuous Intravenous Infusion | Continuous | 20,000 Units/24 hours to 40,000 Units/24 hours

2.4 Pediatric Use

There are no adequate and well-controlled studies on heparin use in pediatric patients. Pediatric dosing recommendations are based on clinical experience. In general, the following dosage schedule may be used as a guideline in pediatric patients:

Initial Dose | 75 units/kg to 100 units/kg (intravenous bolus over 10 minutes)
Maintenance Dose | Infants: 25 units/kg/hour to 30 units/kg/hour (continuous intravenous infusion); Infants less than 2 months have the highest requirements (average 28 units/kg/hour) Children greater than 1 year of age: 18 units/kg/hour to 20 units/kg/hour (continuous intravenous infusion); Older children may require less heparin, similar to weight-adjusted adult dosage.
Monitoring | Adjust heparin to maintain APTT of 60 seconds to 85 seconds, assuming this reflects an anti-Factor Xa level of 0.35 to 0.70.

2.5 Cardiovascular Surgery

Patients undergoing total body perfusion for open-heart surgery should receive an initial dose of not less than 150 units of heparin sodium per kilogram of body weight. Frequently, a dose of 300 units per kilogram is used for procedures estimated to last less than 60 minutes or 400 units per kilogram for those estimated to last longer than 60 minutes.

2.6 Converting to Warfarin

To ensure continuous anticoagulation when converting from heparin sodium to warfarin, continue full heparin therapy for several days until the INR (prothrombin time) has reached a stable therapeutic range. Heparin therapy may then be discontinued without tapering [see Drug Interactions (7.5)].

2.7 Converting to Oral Anticoagulants Other Than Warfarin

For patients currently receiving intravenous heparin, stop intravenous infusion of heparin sodium immediately after administering the first dose of oral anticoagulant; or for intermittent intravenous administration of heparin sodium, start oral anticoagulant 0 to 2 hours before the time that the next dose of heparin was to have been administered.

2.8 Extracorporeal Dialysis

Follow equipment manufacturer's operating directions carefully. A dose of 25 units/kg to 30 units/kg followed by an infusion rate of 1,500 units/hour to 2,000 units/hour is suggested based on pharmacodynamic data if specific manufacturers' recommendations are not available.

3 DOSAGE FORMS AND STRENGTHS

HEPARIN SODIUM IN 0.45% SODIUM CHLORIDE INJECTION is available as:

- Injection: 25,000 USP Units/250 mL (100 USP Units/mL) in clear solution in single-dose flexible plastic container
- Injection: 12,500 USP Units/250 mL (50 USP Units/mL) in clear solution in single-dose flexible plastic container
- Injection: 25,000 USP Units/500 mL (50 USP Units/mL) in clear solution in single-dose flexible plastic container

4 CONTRAINDICATIONS

The use of heparin sodium is contraindicated in patients:

- With history of heparin-induced thrombocytopenia (HIT) (With or Without Thrombosis) [see Warnings and Precautions (5.3)]
- With a known hypersensitivity to heparin or pork products (e.g., anaphylactoid reactions) [see Adverse Reactions (6.1)]
- In whom suitable blood coagulation tests (e.g., the whole blood clotting time, partial thromboplastin time, etc.) cannot be performed at appropriate intervals (this contraindication refers to full-dose heparin; there is usually no need to monitor coagulation parameters in patients receiving low-dose heparin) [see Warnings and Precautions (5.6)]
- With an uncontrollable active bleeding state [see Warnings and Precautions (5.6)], except when treating disseminated intravascular coagulation

5 WARNINGS AND PRECAUTIONS

5.1 Fatal Medication Errors

Do not use this product as a "catheter lock flush" product. Heparin is supplied in various strengths. Fatal hemorrhages have occurred due to medication errors. Carefully examine all heparin products to confirm the correct container choice prior to administration of the drug.

5.2 Hemorrhage

Hemorrhage, including fatal events, has occurred in patients receiving heparin sodium. Avoid using heparin in the presence of major bleeding, except when the benefits of heparin therapy outweigh the potential risks.

Hemorrhage can occur at virtually any site in patients receiving heparin. Adrenal hemorrhage (with resultant acute adrenal insufficiency), ovarian hemorrhage, and retroperitoneal hemorrhage have occurred during anticoagulant therapy with heparin [see Adverse Reactions (6.1)]. A higher incidence of bleeding has been reported in patients, particularly women, over 60 years of age [see Clinical Pharmacology (12.3)]. These patients may require a lower dose. An unexplained fall in hematocrit or fall in blood pressure should lead to serious consideration of a hemorrhagic event.

Use heparin sodium with caution in disease states in which there is increased risk of hemorrhage, including:

- Cardiovascular — Subacute bacterial endocarditis. Severe hypertension.
- Surgical — During and immediately following (a) spinal tap or spinal anesthesia or (b) major surgery, especially involving the brain, spinal cord or eye.
- Hematologic — Conditions associated with increased bleeding tendencies, such as hemophilia, thrombocytopenia and some vascular purpuras.
- Patients with hereditary antithrombin III deficiency receiving concurrent antithrombin III therapy – The anticoagulant effect of heparin is enhanced by concurrent treatment with antithrombin III (human) in patients with hereditary antithrombin III deficiency. To reduce the risk of bleeding, reduce the heparin dose during concomitant treatment with antithrombin III (human).
- Gastrointestinal — Ulcerative lesions and continuous tube drainage of the stomach or small intestine.
- Other — Menstruation, liver disease with impaired hemostasis.

5.3 Heparin-induced Thrombocytopenia (HIT) (With or Without Thrombosis)

HIT is a serious immune-mediated reaction resulting from irreversible aggregation of platelets. HIT may progress to the development of venous and arterial thromboses, a condition known as HIT with thrombosis. Thrombotic events may also be the initial presentation for HIT. These serious thromboembolic events include deep vein thrombosis, pulmonary embolism, cerebral vein thrombosis, limb ischemia, stroke, myocardial infarction, thrombus formation on a prosthetic cardiac valve, mesenteric thrombosis, renal arterial thrombosis, skin necrosis, gangrene of the extremities that may lead to amputation, and fatal outcomes.

Once HIT (with or without thrombosis) is diagnosed or strongly suspected, all heparin sodium sources (including heparin flushes) should be discontinued and an alternative anticoagulant used. Future use of heparin sodium, especially within 3 to 6 months following the diagnosis of HIT (with or without thrombosis), and while patients test positive for HIT antibodies, should be avoided.

Thrombocytopenia of any degree should be monitored closely. If the platelet count falls below 100,000/mm^3 or if recurrent thrombosis develops, the heparin product should be promptly discontinued and alternative anticoagulants considered if patients require continued anticoagulation.

Delayed Onset of HIT (With or Without Thrombosis): Heparin-induced Thrombocytopenia (HIT) (With or Without Thrombosis) can occur up to several weeks after the discontinuation of heparin therapy. Patients presenting with thrombocytopenia or thrombosis after discontinuation of heparin should be evaluated for HIT (With or Without Thrombosis).

5.4 Unresponsiveness to Heparin with Concomitant Use With Andexanet Alfa

Unresponsiveness to unfractionated heparin leading to non-prolongation of activated clotting times and serious thrombotic events has occurred when unfractionated heparin was administered after use of andexanet alfa for the reversal of direct Factor Xa inhibitors (apixaban and rivaroxaban). Avoid use of heparin after use of andexanet alfa. Use an alternative anticoagulant to heparin [see Drug Interactions (7.3)].

5.5 Thrombocytopenia

Thrombocytopenia has been reported to occur in patients receiving heparin with a reported incidence of up to 30%. It can occur 2 to 20 days (average 5 to 9) following the onset of heparin therapy. Platelet counts should be obtained at baseline and periodically during heparin administration. Mild thrombocytopenia (count greater than 100,000/mm^3) may remain stable or reverse even if heparin is continued. However, thrombocytopenia of any degree should be monitored closely. If the count falls below 100,000/mm^3 or if recurrent thrombosis develops, the heparin product should be discontinued, and, if necessary, an alternative anticoagulant administered [see Warnings and Precautions (5.3)].

5.6 Coagulation Testing and Monitoring

When heparin sodium is administered in therapeutic amounts, its dosage should be monitored by frequent blood coagulation tests. If the coagulation test is unduly prolonged or if hemorrhage occurs, heparin sodium should be discontinued promptly [see Overdosage (10)]. Periodic platelet counts, hematocrits and tests for occult blood in stool are recommended during the entire course of heparin therapy [see Dosage and Administration (2.2)].

5.7 Heparin Resistance

Increased resistance to heparin is frequently encountered in fever, thrombosis, thrombophlebitis, infections with thrombosing tendencies, myocardial infarction, cancer and in postsurgical patients, and patients with antithrombin III deficiency. Close monitoring of coagulation tests is recommended in these cases. Adjustment of heparin doses based on anti-Factor Xa levels may be warranted.

5.8 Hypersensitivity Reactions

Patients with documented hypersensitivity to heparin should be given the drug only in clearly life-threatening situations [see Adverse Reactions (6.1)].

Because heparin sodium is derived from animal tissue, monitor for signs and symptoms of hypersensitivity when it is used in patients with a history of allergy.

5.9 Hyperkalemia

Heparin can suppress adrenal secretion of aldosterone leading to hyperkalemia, particularly in patients with diabetes mellitus, chronic renal failure, pre-existing metabolic acidosis, a raised plasma potassium, or taking potassium sparing drugs. The risk of hyperkalemia appears to increase with duration of therapy but is usually reversible upon discontinuation of heparin.

Measure blood potassium in patients at risk of hyperkalemia before starting heparin therapy and periodically in all patients treated for more than 5 days or earlier as deemed fit by the clinician.

6 ADVERSE REACTIONS

The following clinically significant adverse reactions are described elsewhere in the labeling:

- Fatal Medication Errors [see Warnings and Precautions (5.1)]
- Hemorrhage [see Warnings and Precautions (5.2)]
- Heparin-induced Thrombocytopenia (HIT) (With or Without Thrombosis) [see Warnings and Precautions (5.3)]
- Thrombocytopenia [see Warnings and Precautions (5.5)]
- Heparin Resistance [see Warnings and Precautions (5.7)]
- Hypersensitivity Reactions [see Warnings and Precautions (5.8)]
- Hyperkalemia [see Warnings and Precautions (5.9)]

6.1 Postmarketing Experience

The following adverse reactions have been identified during post-approval use of heparin sodium. Because these reactions are reported voluntarily from a population of uncertain size, it is not always possible to reliably estimate their frequency or establish a causal relationship to drug exposure.

Hemorrhage

Hemorrhage is the chief complication that may result from heparin therapy [see Warnings and Precautions (5.2)]. An overly prolonged clotting time or minor bleeding during therapy can usually be controlled by withdrawing the drug [see Overdosage (10)]. Gastrointestinal or urinary tract bleeding during anticoagulant therapy may indicate the presence of an underlying occult lesion. Bleeding can occur at any site but certain specific hemorrhagic complications may be difficult to detect:

a. Adrenal hemorrhage, with resultant acute adrenal insufficiency, has occurred during anticoagulant therapy. Therefore, such treatment should be discontinued in patients who develop signs and symptoms of acute adrenal hemorrhage and insufficiency. Initiation of corrective therapy should not depend on laboratory confirmation of the diagnosis, since any delay in an acute situation may result in the patient's death.
b. Ovarian (corpus luteum) hemorrhage developed in a number of women of reproductive age receiving short- or long-term anticoagulant therapy. This complication if unrecognized may be fatal.
c. Retroperitoneal hemorrhage.

Thrombocytopenia, Heparin-induced Thrombocytopenia (HIT) (With or Without Thrombosis) and Delayed Onset of HIT (With or Without Thrombosis): [see Warnings and Precautions (5.3, 5.5)]

Local Irritation

Local irritation, erythema, mild pain, hematoma or ulceration may follow deep subcutaneous (intrafat) injection of heparin sodium. These complications are much more common after intramuscular use, and such use is not recommended.

Hypersensitivity

Generalized hypersensitivity reactions have been reported with chills, fever, and urticaria as the most usual manifestations, and asthma, rhinitis, lacrimation, headache, nausea and vomiting, and anaphylactoid reactions, including shock, occurring more rarely. Itching and burning, especially on the plantar site of the feet, may occur [see Warnings and Precautions (5.8)].

Episodes of painful, ischemic, and cyanosed limbs have been reported with heparin use.

Metabolism and Nutrition Disorders – Hyperkalemia.

Elevations of Serum Aminotransferases

Significant elevations of aspartate aminotransferase (AST) and alanine aminotransferase (ALT) levels have occurred in a high percentage of patients (and healthy subjects) who have received heparin.

Others

Osteoporosis following long-term administration of high doses of heparin, cutaneous necrosis after systemic administration, suppression of aldosterone synthesis, delayed transient alopecia, priapism, and rebound hyperlipemia on discontinuation of heparin sodium have also been reported.

Reactions which may occur because of the solution or the technique of administration include febrile response, infection at the site of injection, venous thrombosis or phlebitis extending from the site of injection, extravasation, and hypervolemia.

7 DRUG INTERACTIONS

7.1 Oral Anticoagulants

Heparin sodium may prolong the one-stage prothrombin time. Therefore, when heparin sodium is given with dicumarol or warfarin sodium, a period of at least 5 hours after the last intravenous dose or 24 hours after the last subcutaneous dose should elapse before blood is drawn if a valid prothrombin time is to be obtained.

7.2 Platelet Inhibitors

Drugs such as acetylsalicylic acid, dextran, phenylbutazone, ibuprofen, indomethacin, dipyridamole, hydroxychloroquine and others that interfere with platelet-aggregation reactions (the main hemostatic defense of heparinized patients) may induce bleeding and should be used with caution in patients receiving heparin sodium.

7.3 Unresponsiveness to Heparin With Concomitant Use With Andexanet Alfa

Andexanet binds to heparin-bound antithrombin III (ATIII) and may reduce the anticoagulant effect of heparin. Unresponsiveness to unfractionated heparin may lead to serious and life-threatening thrombotic events. Use of andexanet alfa as an antidote for heparin has not been established. Avoid use of heparin after use of andexanet alfa for the reversal of direct Factor Xa inhibitors (apixaban and rivaroxaban). If anticoagulation is needed, use an alternative anticoagulant to heparin [see Warnings and Precautions (5.4)].

7.4 Other Interactions

Digitalis, tetracyclines, nicotine, or antihistamines, or intravenous nitroglycerin may partially counteract the anticoagulant action of heparin sodium. Intravenous nitroglycerin administered to heparinized patients may result in a decrease of the partial thromboplastin time with subsequent rebound effect upon discontinuation of nitroglycerin. Careful monitoring of partial thromboplastin time and adjustment of heparin dosage are recommended during coadministration of heparin and intravenous nitroglycerin.

7.5 Drug/Laboratory Tests Interactions

Prothrombin time – Heparin sodium may prolong the one-stage prothrombin time. Therefore, when heparin sodium is given with warfarin, allow a period of at least 5 hours after the last intravenous dose or 24 hours after the last subcutaneous dose of heparin to elapse before blood is drawn to obtain a valid prothrombin time.

Hyperaminotransferasemia

Significant elevations of aminotransferase AST (SGOT) and ALT (SGPT) levels have occurred in a high percentage of patients (and healthy subjects) who have received heparin. Since aminotransferase determinations are important in the differential diagnosis of myocardial infarction, liver disease and pulmonary emboli, rises that might be caused by drugs (like heparin) should be interpreted with caution.

8 USE IN SPECIFIC POPULATIONS

8.1 Pregnancy

Risk Summary

There are no available data on HEPARIN SODIUM IN SODIUM CHLORIDE INJECTION use in pregnant women to inform a drug-associated risk of major birth defects and miscarriage. In published reports, heparin exposure during pregnancy did not show evidence of an increased risk of adverse maternal or fetal outcomes in humans. No teratogenicity, but early embryo-fetal death was observed in animal reproduction studies with administration of heparin sodium to pregnant rats and rabbits during organogenesis at doses up to 10,000 USP Units/kg/day, approximately 10 times the maximum recommended human dose (MRHD) of 40,000 USP Units/24 hours infusion (see Data). Consider the benefits and risks of HEPARIN SODIUM IN SODIUM CHLORIDE INJECTION to a pregnant woman and possible risks to the fetus when prescribing HEPARIN SODIUM IN SODIUM CHLORIDE INJECTION.

The estimated background risk of major birth defects and miscarriage for the indicated population is unknown. All pregnancies have a risk of birth defect, loss, or other adverse outcomes. In the U.S. general population, the estimated background risk of major birth defects and miscarriage in clinically recognized pregnancies is 2-4% and 15-20%, respectively.

Data

Human Data

The maternal and fetal outcomes associated with uses of heparin via various dosing methods and administration routes during pregnancy have been investigated in numerous studies. These studies generally reported normal deliveries with no maternal or fetal bleeding and no other complications.

Animal Data

In a published study conducted in rats and rabbits, pregnant animals received heparin intravenously during organogenesis at a dose of 10,000 USP Units/kg/day, approximately 10 times the maximum human daily dose based on body weight. The number of early resorptions increased in both species. There was no evidence of teratogenic effects.

8.2 Lactation

Risk Summary

There is no information regarding the presence of HEPARIN SODIUM IN SODIUM CHLORIDE INJECTION in human milk, the effects on the breastfed child, or the effects on milk production. Due to its large molecular weight, heparin is not likely to be excreted in human milk, and any heparin in milk would not be orally absorbed by a nursing child. The developmental and health benefits of breastfeeding should be considered along with the mother's clinical need for HEPARIN SODIUM IN SODIUM CHLORIDE INJECTION and any potential adverse effects on the breastfed child from HEPARIN SODIUM IN SODIUM CHLORIDE INJECTION or from the underlying maternal condition [see Use in Specific Populations (8.4)].

8.4 Pediatric Use

There are no adequate and well-controlled studies on heparin use in pediatric patients. Pediatric dosing recommendations are based on clinical experience [see Dosage and Administration (2.4)].

8.5 Geriatric Use

A higher incidence of bleeding has been reported in patients over 60 years of age, especially women [see Warnings and Precautions (5.2)]. Lower doses of heparin may be indicated in these patients [see Clinical Pharmacology (12.3)].

10 OVERDOSAGE

Symptoms

Bleeding is the chief sign of heparin overdosage. Nosebleeds, blood in urine or tarry stools may be noted as the first sign of bleeding. Easy bruising or petechial formations may precede frank bleeding.

Treatment

Neutralization of heparin effect:

When clinical circumstances (bleeding) require reversal of heparinization, protamine sulfate (1% solution) by slow infusion will neutralize heparin sodium. No more than 50 mg should be administered, very slowly in any 10-minute period. Each mg of protamine sulfate neutralizes approximately 100 USP Heparin Units. The amount of protamine required decreases over time as heparin is metabolized. Although the metabolism of heparin is complex, it may, for the purpose of choosing a protamine dose, be assumed to have a half-life of about ½ hour after intravenous injection.

Administration of protamine sulfate can cause severe hypotensive and anaphylactoid reactions. Because fatal reactions often resembling anaphylaxis have been reported, the drug should be given only when resuscitation techniques and treatment of anaphylactoid shock are readily available.

For additional information, the labeling of Protamine Sulfate Injection, USP products should be consulted.

Consider contacting the Poison Help line (1-800-222-1222) or a medical toxicologist for additional overdose management recommendations.

11 DESCRIPTION

Heparin is a heterogeneous group of straight-chain anionic mucopolysaccharides, called glycosaminoglycans possessing anticoagulant properties. It is composed of polymers of alternating derivations of α-D-glucosamido (N-Sulfated O-Sulfated or N-acetylated) and O-sulfated uronic acid (α-L-iduronic acid or β-D-glucoronic acid).

Structure of Heparin Sodium (representative subunits):

HEPARIN SODIUM IN SODIUM CHLORIDE INJECTION is a sterile preparation of heparin sodium (derived from porcine intestinal mucosa) for intravenous administration. It contains no bacteriostatic or antimicrobial agent or added buffer. The solution may contain sodium hydroxide and/or hydrochloric acid for pH adjustment. The pH range is 6.1 (5.0 – 7.5) and the osmolarity mOsmol/L (calc.) is 155. The potency is determined by a biological assay using a USP reference standard based on units of heparin activity per milligram.

Each mL of the 50 USP Units per mL preparations contains: 50 USP Units of heparin sodium, 4.5 mg sodium chloride and 0.1 mg edetate disodium, anhydrous added as a stabilizer.

Each mL of the 100 USP Units per mL preparations contains: 100 USP Units of heparin sodium, 4.5 mg sodium chloride and 0.1 mg edetate disodium, anhydrous added as a stabilizer.

12 CLINICAL PHARMACOLOGY

12.1 Mechanism of Action

Heparin inhibits reactions that lead to the clotting of blood and the formation of fibrin clots both in vitro and in vivo. Heparin acts at multiple sites in the normal coagulation system. Small amounts of heparin in combination with antithrombin III (heparin cofactor) can inhibit thrombosis by inactivating activated Factor X and inhibiting the conversion of prothrombin to thrombin. Once active thrombosis has developed, larger amounts of heparin can inhibit further coagulation by inactivating thrombin and preventing the conversion of fibrinogen to fibrin. Heparin also prevents the formation of a stable fibrin clot by inhibiting the activation of the fibrin stabilizing factor. Heparin does not have fibrinolytic activity; therefore, it will not lyse existing clots.

12.2 Pharmacodynamics

Bleeding time is usually unaffected by heparin. Clotting time is prolonged by full therapeutic doses of heparin; in most cases it is not measurably affected by low doses of heparin.

12.3 Pharmacokinetics

Absorption

Heparin is not absorbed through gastrointestinal tract and therefore administered via parenteral route. Peak plasma concentration and the onset of action are achieved immediately after intravenous administration.

Distribution

Heparin is highly bound to antithrombin, fibrinogens, globulins, serum proteases and lipoproteins. The volume of distribution is 0.07 L/kg.

Elimination

Metabolism

Heparin does not undergo enzymatic degradation.

Excretion

Heparin is mainly cleared from the circulation by liver and reticuloendothelial cells mediated uptake into extravascular space. Heparin undergoes biphasic clearance, a) rapid saturable clearance (zero order process due to binding to proteins, endothelial cells and macrophage) and b) slower first order elimination. The plasma half-life is dose-dependent, and it ranges from 0.5 to 2 h.

Specific Populations

Geriatric patients

Patients over 60 years of age, following similar doses of heparin, may have higher plasma levels of heparin and longer activated partial thromboplastin times (APTTs) compared with patients under 60 years of age [see Use in Specific Populations (8.5)].

13 NONCLINICAL TOXICOLOGY

13.1 Carcinogenesis, Mutagenesis, Impairment of Fertility

Long-term studies in animals to evaluate the carcinogenic potential, reproduction studies in animals to determine effects on fertility of males and females, and the studies to determine mutagenic potential have not been conducted.

16 HOW SUPPLIED/STORAGE AND HANDLING

HEPARIN SODIUM IN 0.45% SODIUM CHLORIDE INJECTION is a clear solution and is supplied in single-dose flexible plastic containers in varied sizes and concentrations as shown in the accompanying Table.

Unit of Sale | Concentration
NDC 0409-7650-62; Case of 24 Single-dose flexible plastic containers | 25,000 USP Units/250 mL; (100 USP Units/mL)
NDC 0409-7650-30; Case of 30 Single-dose flexible plastic containers | 25,000 USP Units/250 mL; (100 USP Units/mL)
NDC 0409-7651-62; Case of 24 Single-dose flexible plastic containers | 12,500 USP Units/250 mL; (50 USP Units/mL)
NDC 0409-0012-30; Case of 30 Single-dose flexible plastic containers | 12,500 USP Units/250 mL; (50 USP Units/mL)
NDC 0409-7651-03; Case of 24 Single-dose flexible plastic containers | 25,000 USP Units/500 mL; (50 USP Units/mL)
NDC 0409-3150-20; Case of 20 Single-dose flexible plastic containers | 25,000 USP Units/500 mL; (50 USP Units/mL)

Store at 20°C to 25°C (68°F to 77°F). [See USP Controlled Room Temperature.] Protect from freezing.

17 PATIENT COUNSELING INFORMATION

Hemorrhage

Inform patients that it may take them longer than usual to stop bleeding, that they may bruise and/or bleed more easily when they are treated with heparin, and that they should report any unusual bleeding or bruising to their physician. Hemorrhage can occur at virtually any site in patients receiving heparin. Fatal hemorrhages have occurred [see Warnings and Precautions (5.2)].

Prior to Surgery

Advise patients to inform physicians and dentists that they are receiving heparin before any surgery is scheduled [see Warnings and Precautions (5.2)].

Heparin-Induced Thrombocytopenia

Inform patients of the risk of heparin-induced thrombocytopenia (HIT). HIT may progress to the development of venous and arterial thromboses, a condition known as heparin-induced thrombocytopenia and thrombosis (HITT). HIT (With or Without Thrombosis) can occur up to several weeks after the discontinuation of heparin therapy [see Warnings and Precautions (5.3, 5.5)].

Hypersensitivity

Inform patients that generalized hypersensitivity reactions have been reported. Necrosis of the skin has been reported at the site of subcutaneous injection of heparin [see Warnings and Precautions (5.8), Adverse Reactions (6.1)].

Other Medications

Because of the risk of hemorrhage, advise patients to inform their physicians and dentists of all medications they are taking, including non-prescription medications, and before starting any new medication [see Drug Interactions (7.2)].

This product's labeling may have been updated. For the most recent prescribing information, please visit www.pfizer.com.

For medical information about HEPARIN SODIUM IN SODIUM CHLORIDE INJECTION, please visit www.pfizermedinfo.com or call 1-800-438-1985.

Distributed by Hospira, Inc., Lake Forest, IL 60045 USA

LAB-1392-6.0

PRINCIPAL DISPLAY PANEL - 250 mL Bag Label - 7650

250 mL
NDC 0409-7650-52

HEPARIN SODIUM

25,000 USP Units
per 250 mL
(100 USP Units/mL)
in 0.45% Sodium Chloride Injection

EACH 100 mL CONTAINS HEPARIN
SODIUM 10,000 USP UNITS (PORCINE
INTESTINAL MUCOSA); SODIUM
CHLORIDE 0.45 g; EDETATE DISODIUM,
ANHYDROUS 10 mg ADDED AS STABILIZER.
MAY CONTAIN SODIUM HYDROXIDE
AND/OR HYDROCHLORIC ACID FOR pH
ADJUSTMENT. STERILE. NOT MADE WITH
NATURAL RUBBER LATEX.
USUAL DOSAGE: SEE INSERT.

ADDITIVES SHOULD NOT
BE MADE TO THIS SOLUTION.

SINGLE DOSE CONTAINER. DISCARD
UNUSED PORTION. FOR INTRAVENOUS
USE ONLY.

Rx only

3
V
CONTAINS DEHP

IM-3954

HOSPIRA, INC., LAKE FOREST, IL 60045 USA

Hospira

PRINCIPAL DISPLAY PANEL - 250 mL Bag Overwrap - 7650

2
HDPE

TO OPEN TEAR AT NOTCH

DO NOT REMOVE FROM OVERWRAP UNTIL READY FOR USE. AFTER REMOVING
THE OVERWRAP, CHECK FOR MINUTE LEAKS BY SQUEEZING CONTAINER FIRMLY.
IF LEAKS ARE FOUND, DISCARD SOLUTION AS STERILITY MAY BE IMPAIRED.
RECOMMENDED STORAGE: ROOM TEMPERATURE (25°C). AVOID EXCESSIVE
HEAT. PROTECT FROM FREEZING. SEE INSERT.

98-4321-R14-3/98

PRINCIPAL DISPLAY PANEL - 250 mL Bag Label - 7651

250 mL
NDC 0409-7651-52

12,500 USP Units / 250 mL
(50 USP Units / mL)

Heparin Sodium in
0.45% Sodium Chloride Injection

EACH 100 mL CONTAINS HEPARIN SODIUM
5,000 USP UNITS (PORCINE INTESTINAL
MUCOSA); SODIUM CHLORIDE 0.45 g;
EDETATE DISODIUM, ANHYDROUS
10 mg ADDED AS STABILIZER. MAY
CONTAIN SODIUM HYDROXIDE AND/OR
HYDROCHLORIC ACID FOR pH ADJUSTMENT.
STERILE. NOT MADE WITH NATURAL
RUBBER LATEX. USUAL DOSAGE: SEE INSERT.

ADDITIVES SHOULD NOT BE MADE
TO THIS SOLUTION.

SINGLE DOSE CONTAINER. DISCARD
UNUSED PORTION. FOR INTRAVENOUS USE
ONLY.

Rx ONLY

3
V
CONTAINS DEHP

Hospira

IM-3959

HOSPIRA, INC., LAKE FOREST, IL 60045 USA

PRINCIPAL DISPLAY PANEL - 250 mL Bag Overwrap - 7651

2
HDPE

TO OPEN TEAR AT NOTCH

DO NOT REMOVE FROM OVERWRAP UNTIL READY FOR USE. AFTER REMOVING
THE OVERWRAP, CHECK FOR MINUTE LEAKS BY SQUEEZING CONTAINER FIRMLY.
IF LEAKS ARE FOUND, DISCARD SOLUTION AS STERILITY MAY BE IMPAIRED.
RECOMMENDED STORAGE: ROOM TEMPERATURE (25°C). AVOID EXCESSIVE
HEAT. PROTECT FROM FREEZING. SEE INSERT.

98-4321-R14-3/98

PRINCIPAL DISPLAY PANEL - 500 mL Bag Label - 7651

500 mL
25,000 USP Units / 500 mL
(50 USP Units / mL)
NDC 0409-7651-13

Heparin Sodium in
0.45% Sodium Chloride Injection

EACH 100 mL CONTAINS HEPARIN SODIUM 5,000 USP
UNITS (PORCINE INTESTINAL MUCOSA); SODIUM
CHLORIDE 0.45 g; EDETATE DISODIUM, ANHYDROUS
10 mg ADDED AS STABILIZER. MAY CONTAIN SODIUM
HYDROXIDE AND/OR HYDROCHLORIC ACID FOR
pH ADJUSTMENT. STERILE. NOT MADE WITH NATURAL
RUBBER LATEX. USUAL DOSAGE: SEE INSERT.

ADDITIVES SHOULD NOT BE MADE TO THIS SOLUTION.

SINGLE DOSE CONTAINER. DISCARD UNUSED PORTION.
FOR INTRAVENOUS USE ONLY.

Rx ONLY

3
V
CONTAINS DEHP

IM-3958

HOSPIRA, INC., LAKE FOREST, IL 60045 USA

Hospira

PRINCIPAL DISPLAY PANEL - 500 mL Bag Overwrap - 7651

2
HDPE

TO OPEN TEAR AT NOTCH

DO NOT REMOVE FROM OVERWRAP UNTIL READY FOR USE. AFTER REMOVING
THE OVERWRAP, CHECK FOR MINUTE LEAKS BY SQUEEZING CONTAINER FIRMLY.
IF LEAKS ARE FOUND, DISCARD SOLUTION AS STERILITY MAY BE IMPAIRED.
RECOMMENDED STORAGE: ROOM TEMPERATURE (25°C). AVOID EXCESSIVE
HEAT. PROTECT FROM FREEZING. SEE INSERT.

98-4321-R14-3/98

PRINCIPAL DISPLAY PANEL - 500 mL Bag Label - 3150

500mL
NDC 0409-3150-05

25,000 USP Units / 500 mL
(50 USP Units / mL)

Heparin Sodium
25,000 USP Units / 500 mL
(50 USP Units / mL)
in 0.45% Sodium Chloride Injection

Each 100 mL contains Heparin Sodium 5,000 USP Units
(Porcine Intestinal Mucosa); Sodium Chloride 0.45 g; Edetate
Disodium, Anhydrous 10 mg added as stabilizer. May contain Sodium
Hydroxide and/or Hydrochloric Acid for pH adjustment.
Sterile. Not made with natural rubber latex.
Recommended dosage: See prescribing information.
Additives should not be made to this solution.
Single dose container. Discard unused portion.
For Intravenous Use only. Inspect bag by squeezing firmly. If leaks are found,
discard. Store at 20℃ to 25℃ (68℉ to 77℉). [See USP Controlled
Room Temperature.] Protect from freezing.
Do not remove from overwrap until ready for use.

Rx ONLY

5
PP

Distributed by Hospira, Inc.,
Lake Forest, IL 60045 USA

Hospira

PRINCIPAL DISPLAY PANEL - 250 mL Bag Label - 7650

250mL
NDC 0409-7650-05

Heparin Sodium
25,000 USP Units / 250 mL
(100 USP Units / mL)
in 0.45% Sodium Chloride Injection

Each 100 mL contains Heparin Sodium 10,000 USP Units (Porcine
Intestinal Mucosa); Sodium Chloride 0.45 g; Edetate Disodium,
Anhydrous 10 mg added as stabilizer. May contain Sodium
Hydroxide and/or Hydrochloric Acid for pH adjustment.
Sterile. Not made with natural rubber latex.
Recommended dosage: See prescribing information.
Additives should not be made to this solution.
Single dose container. Discard unused portion.
For Intravenous Use only.
Check for minute leaks. If leaks are found, discard.
Store at 20℃ to 25℃ (68℉ to 77℉). [See USP Controlled Room
Temperature.] Protect from freezing.
Do not remove from overwrap until ready for use.
Distributed by Hospira, Inc., Lake Forest, IL 60045 USA

Rx ONLY

5
PP

Hospira

PRINCIPAL DISPLAY PANEL - 250 mL Bag Label - 0012

250mL
NDC 0409-0012-02
12,500 USP Units / 250 mL
(50 USP Units / mL)

Heparin Sodium in
0.45% Sodium Chloride Injection

Each 100 mL contains Heparin Sodium 5,000 USP Units
(Porcine Intestinal Mucosa); Sodium Chloride 0.45 g;
Edetate Disodium, Anhydrous 10 mg added as stabilizer.
May contain Sodium Hydroxide and/or Hydrochloric Acid
for pH adjustment.
Sterile. Not made with natural rubber latex.
Recommended dosage: See prescribing information.
Additives should not be made to this solution.
Single dose container. Discard unused portion.
For Intravenous Use only.
Check for minute leaks. If leaks are found, discard.
Store at 20℃ to 25℃ (68℉ to 77℉). [See USP Controlled
Room Temperature.] Protect from freezing.
Do not remove from overwrap until ready for use.
Distributed by Hospira, Inc., Lake Forest, IL 60045 USA

Rx ONLY

5
PP

Hospira